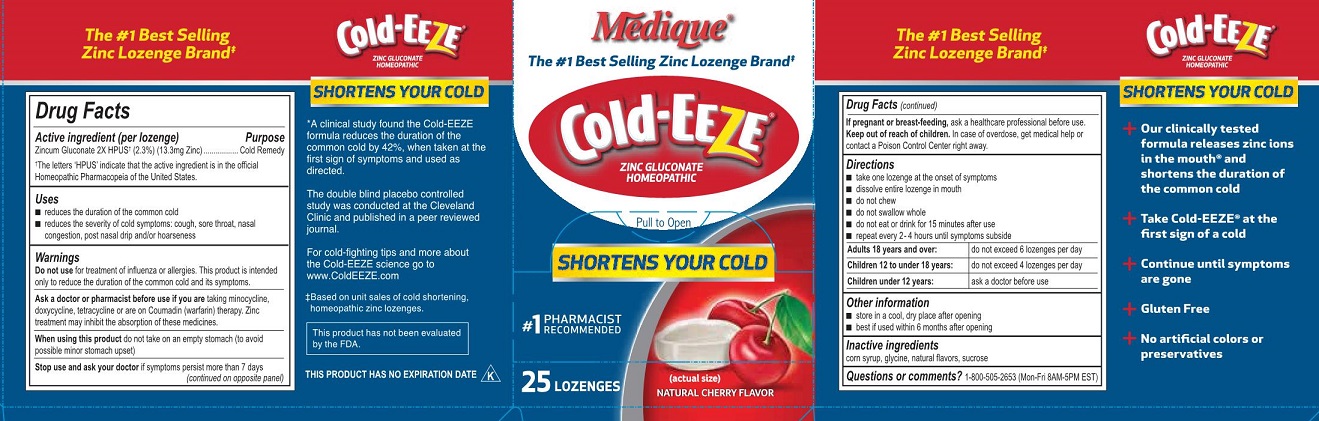 DRUG LABEL: Medique Cold Eeze
NDC: 47682-478 | Form: LOZENGE
Manufacturer: Unifirst First Aid Corporation
Category: homeopathic | Type: HUMAN OTC DRUG LABEL
Date: 20250909

ACTIVE INGREDIENTS: ZINC GLUCONATE 2 [hp_X]/1 1
INACTIVE INGREDIENTS: CORN SYRUP; SUCROSE; GLYCINE

Medique Cold-Eeze

Active ingredient

Zincum Gluconicum 2x HPUS†(13.3mg Zinc)
†The letters ‘HPUS’ indicate that the active ingredient is in the official Homeopathic Pharmacopeia of the United States.

Purpose

Cold Remedy

Uses

- to reduce the duration of the common cold
- reduces the severity of cold symptoms: cough, sore throat, nasal congestion, post nasal drip and/or hoarseness

Warnings

Do not use for the treatment of influenza or allergies. This product is intended only to reduce the duration of the common cold and its symptoms.

Ask a doctor or pharmacist before use if you are taking minocycline, doxycycline, tetracycline, or are on Coumadin (warfarin) therapy. Zinc treatment may inhibit the absorption of these medicines.

When using this product do not take on an empty stomach (to avoid possible minor stomach upset).

Stop use and ask a doctor if symptoms persist beyond 7 days.

PREGNANCY OR BREAST FEEDING

If pregnant or breast-feeding, ask a healthcare professional before use.

Keep out of reach of children. In case of overdose, get medical help or contact a Poison Control Center right away.

Directions

- take one lozenge at the onset of symptoms
- dissolve entire lozenge in mouth
- do not chew
- do not swallow whole
- do not eat or drink for 15 minutes after use
- repeat every 2-4 hours until symptoms subside

Adults and children 18 years and over: do not exceed 6 lozenges per day

Children 12 to 18 years: do not exceed 4 lozenges per day

Children under 12 years: ask a doctor before use

Other information

- store in cool, dry place after opening;
- best if used within 6 months after opening

Inactive ingredients

corn syrup, glycine, natural flavors, sucrose

Questions or comments?

1-800-505-2653 (Mon-Fri 8AM-5PM EST)

Medique Cold-Eeze Label

Medique®

The # 1 Best Selling Zinc Lozenge Brand

Cold-Eeeze®

Zinc Gluconate

Homeopathic

Pull to Open

Shortens Your Cold

#1 Pharmacist Recommended

25 Lozenges

(actual size)

Natural Cherry Flavor